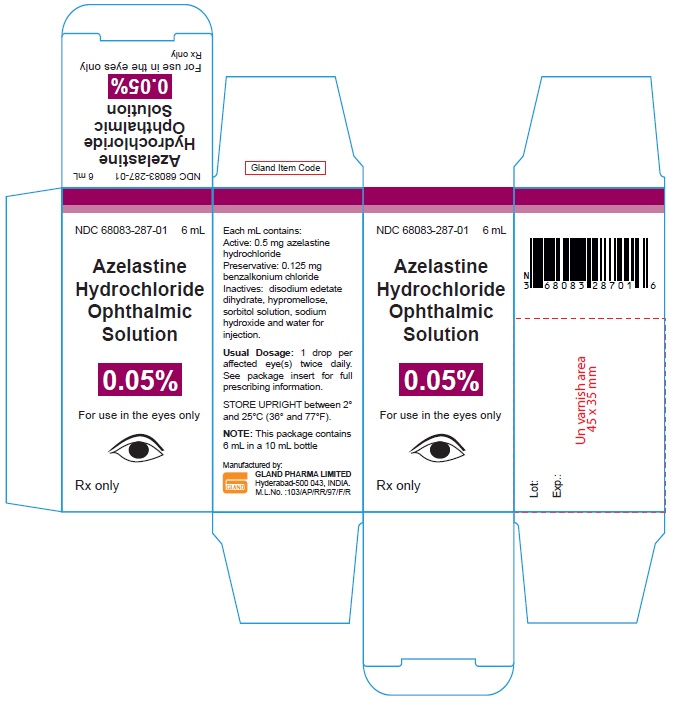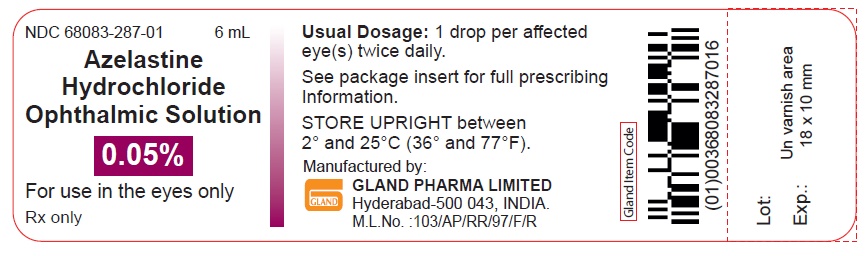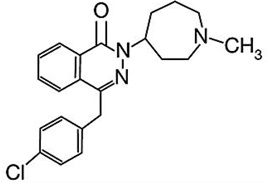 DRUG LABEL: Azelastine Hydrochloride
NDC: 68083-287 | Form: SOLUTION/ DROPS
Manufacturer: Gland Pharma Limited
Category: prescription | Type: Human Prescription Drug Label
Date: 20251022

ACTIVE INGREDIENTS: AZELASTINE HYDROCHLORIDE 0.5 mg/1 mL
INACTIVE INGREDIENTS: BENZALKONIUM CHLORIDE 0.125 mg/1 mL; EDETATE DISODIUM; HYPROMELLOSES; SORBITOL; SODIUM HYDROXIDE; WATER

Azelastine Hydrochloride Ophthalmic Solution, 0.05%

DESCRIPTION

Azelastine hydrochloride ophthalmic solution, 0.05% is a sterile ophthalmic solution containing azelastine hydrochloride, a relatively selective H1-receptor antagonist for topical administration to the eyes. Azelastine hydrochloride is a white crystalline powder with a molecular weight of 418.37. Azelastine hydrochloride is sparingly soluble in water, methanol and propylene glycol, and slightly soluble in ethanol, octanol, and glycerine. Azelastine hydrochloride is a racemic mixture with a melting point of 225°C. The chemical name for azelastine hydrochloride is (±)-1-(2H)-phthalazinone,4-[(4-chlorophenyl)methyl]-2-(hexahydro-1-methyl-1H-azepin-4-yl), monohydrochloride and is represented by the following chemical structure:
Empirical chemical structure: C22 H24ClN3O.HCl
Each mL of azelastine hydrochloride ophthalmic solution contains: Active: 0.5 mg azelastine hydrochloride, equivalent to 0.457 mg of azelastine base; Preservative: 0.125 mg benzalkonium chloride; Inactives: disodium edetate dihydrate, hypromellose, sorbitol solution, sodium hydroxide and water for injection. It has a pH of approximately 5.0 to 6.5 and an osmolarity of approximately 271 to 312 mOsmol/L.

CLINICAL PHARMACOLOGY

Azelastine hydrochloride is a relatively selective histamine H1 antagonist and an inhibitor of the release of histamine and other mediators from cells (e.g. mast cells) involved in the allergic response. Based on in-vitro studies using human cell lines, inhibition of other mediators involved in allergic reactions (e.g. leukotrienes and PAF) has been demonstrated with azelastine hydrochloride. Decreased chemotaxis and activation of eosinophils has also been demonstrated.
Pharmacokinetics and Metabolism
Absorption of azelastine following ocular administration was relatively low. A study in symptomatic patients receiving one drop of azelastine hydrochloride ophthalmic solution in each eye two to four times a day (0.06 to 0.12 mg azelastine hydrochloride) demonstrated plasma concentrations of azelastine hydrochloride to generally be between 0.02 and 0.25 ng/mL after 56 days of treatment. Three of nineteen patients had quantifiable amounts of N-desmethylazelastine that ranged from 0.25 to 0.87 ng/mL at Day 56.
Based on intravenous and oral administration, the elimination half-life, steady-state volume of distribution and plasma clearance were 22 hours, 14.5 L/kg and 0.5 L/h/kg, respectively.

Approximately 75% of an oral dose of radiolabeled azelastine hydrochloride was excreted in the feces with less than 10% as unchanged azelastine. Azelastine hydrochloride is oxidatively metabolized to the principal metabolite, N-desmethylazelastine, by the cytochrome P450 enzyme system. In-vitro studies in human plasma indicate that the plasma protein binding of azelastine and N-desmethylazelastine are approximately 88% and 97%, respectively.
Clinical Trials
In a conjunctival antigen challenge study, azelastine hydrochloride ophthalmic solution was more effective than its vehicle in preventing itching associated with allergic conjunctivitis. Azelastine hydrochloride ophthalmic solution had a rapid (within 3 minutes) onset of effect and a duration of effect of approximately 8 hours for the prevention of itching.
In environmental studies, adult and pediatric patients with seasonal allergic conjunctivitis were treated with azelastine hydrochloride ophthalmic solution for two to eight weeks. In these studies, azelastine hydrochloride ophthalmic solution was more effective than its vehicle in relieving itching associated with allergic conjunctivitis.

INDICATIONS AND USAGE

Azelastine hydrochloride ophthalmic solution is indicated for the treatment of itching of the eye associated with allergic conjunctivitis.

CONTRAINDICATIONS

Azelastine hydrochloride ophthalmic solution is contraindicated in persons with known or suspected hypersensitivity to any of its components.

WARNINGS

Azelastine hydrochloride ophthalmic solution is for topical ophthalmic use only and not for injection or oral use.

PRECAUTIONS

Information for Patients

To prevent contaminating the dropper tip and solution, care should be taken not to touch any surface, the eyelids, or surrounding areas with the dropper tip of the bottle. Keep bottle tightly closed when not in use. This product is sterile when packaged.
Patients should be advised not to wear a contact lens if their eye is red. Azelastine hydrochloride ophthalmic solution should not be used to treat contact lens related irritation. The preservative in azelastine hydrochloride ophthalmic solution, benzalkonium chloride, may be absorbed by soft contact lenses. Patients who wear soft contact lenses and whose eyes are not red, should be instructed to wait at least ten minutes after instilling azelastine hydrochloride ophthalmic solution before they insert their contact lenses.

Carcinogenesis, Mutagenesis, Impairment of Fertility

Azelastine hydrochloride administered orally for 24 months was not carcinogenic in rats and mice at doses up to 30 mg/kg/day and 25 mg/kg/day, respectively. Based on a 30 μL drop size, these doses were approximately 25,000 and 21,000 times higher than the maximum recommended ocular human use level of 0.001 mg/kg/day for a 50 kg adult.
Azelastine hydrochloride showed no genotoxic effects in the Ames test, DNA repair test, mouse lymphoma forward mutation assay, mouse micronucleus test, or chromosomal aberration test in rat bone marrow. Reproduction and fertility studies in rats showed no effects on male or female fertility at oral doses of up to 25,000 times the maximum recommended ocular human use level.

At 68.6 mg/kg/day (57,000 times the maximum recommended ocular human use level), the duration of the estrous cycle was prolonged and copulatory activity and the number of pregnancies were decreased. The numbers of corpora lutea and implantations were decreased; however, the implantation ratio was not affected.

Pregnancy

Teratogenic Effects: Azelastine hydrochloride has been shown to be embryotoxic, fetotoxic, and teratogenic (external and skeletal abnormalities) in mice at an oral dose of 68.6 mg/kg/day (57,000 times the recommended ocular human use level). At an oral dose of 30 mg/kg/day (25,000 times the recommended ocular human use level), delayed ossification (undeveloped metacarpus) and the incidence of 14th rib were increased in rats. At 68.6 mg/kg/day (57,000 times the maximum recommended ocular human use level) azelastine hydrochloride caused resorption and fetotoxic effects in rats. The relevance to humans of these skeletal findings noted at only high drug exposure levels is unknown.
There are no adequate and well-controlled studies in pregnant women. Azelastine hydrochloride ophthalmic solution should be used during pregnancy only if the potential benefit justifies the potential risk to the fetus.

Nursing Mothers

It is not known whether azelastine hydrochloride is excreted in human milk. Because many drugs are excreted in human milk, caution should be exercised when azelastine hydrochloride ophthalmic solution is administered to a nursing woman.

Pediatric Use

Safety and effectiveness in pediatric patients below the age of 3 have not been established.

Geriatric Use

No overall differences in safety or effectiveness have been observed between elderly and younger adult patients.

ADVERSE REACTIONS

In controlled multiple-dose studies where patients were treated for up to 56 days, the most frequently reported adverse reactions were transient eye burning/stinging (approximately 30%), headaches (approximately 15%) and bitter taste (approximately 10%). The occurrence of these events was generally mild.
The following events were reported in 1 to 10% of patients: asthma, conjunctivitis, dyspnea, eye pain, fatigue, influenza-like symptoms, pharyngitis, pruritus, rhinitis and temporary blurring. Some of these events were similar to the underlying disease being studied.

To report SUSPECTED ADVERSE REACTIONS, contact Gland Pharma at 866-770-7144 or FDA at 1-800-FDA-1088 or www.fda.gov/medwatch.

DOSAGE AND ADMINISTRATION

The recommended dose is one drop instilled into each affected eye twice a day.

HOW SUPPLIED

Azelastine hydrochloride ophthalmic solution, 0.05% is supplied as follows:
6 mL (NDC#68083-287-01) solution in a 10 mL LDPE container with a LDPE dropper tip and a white HDPE screw cap.
Storage
Store UPRIGHT between 2° and 25°C (36° and 77°F).
Rx only
Manufactured by
Gland Pharma Limited
D.P.Pally, Dundigal Post
Hyderabad - 500043, INDIA.

Revised: 10/2025

PACKAGE LABEL.PRINCIPAL DISPLAY PANEL

Container Label:
NDC 68083-287-01 6 mL
Azelastine

Hydrochloride

Ophthalmic Solution
0.05%
For use in the eyes only
Rx only
Carton Label:
NDC 68083-287-01 6 mL

Azelastine
Hydrochloride
Ophthalmic
Solution
0.05%

For use in the eyes only
Rx only